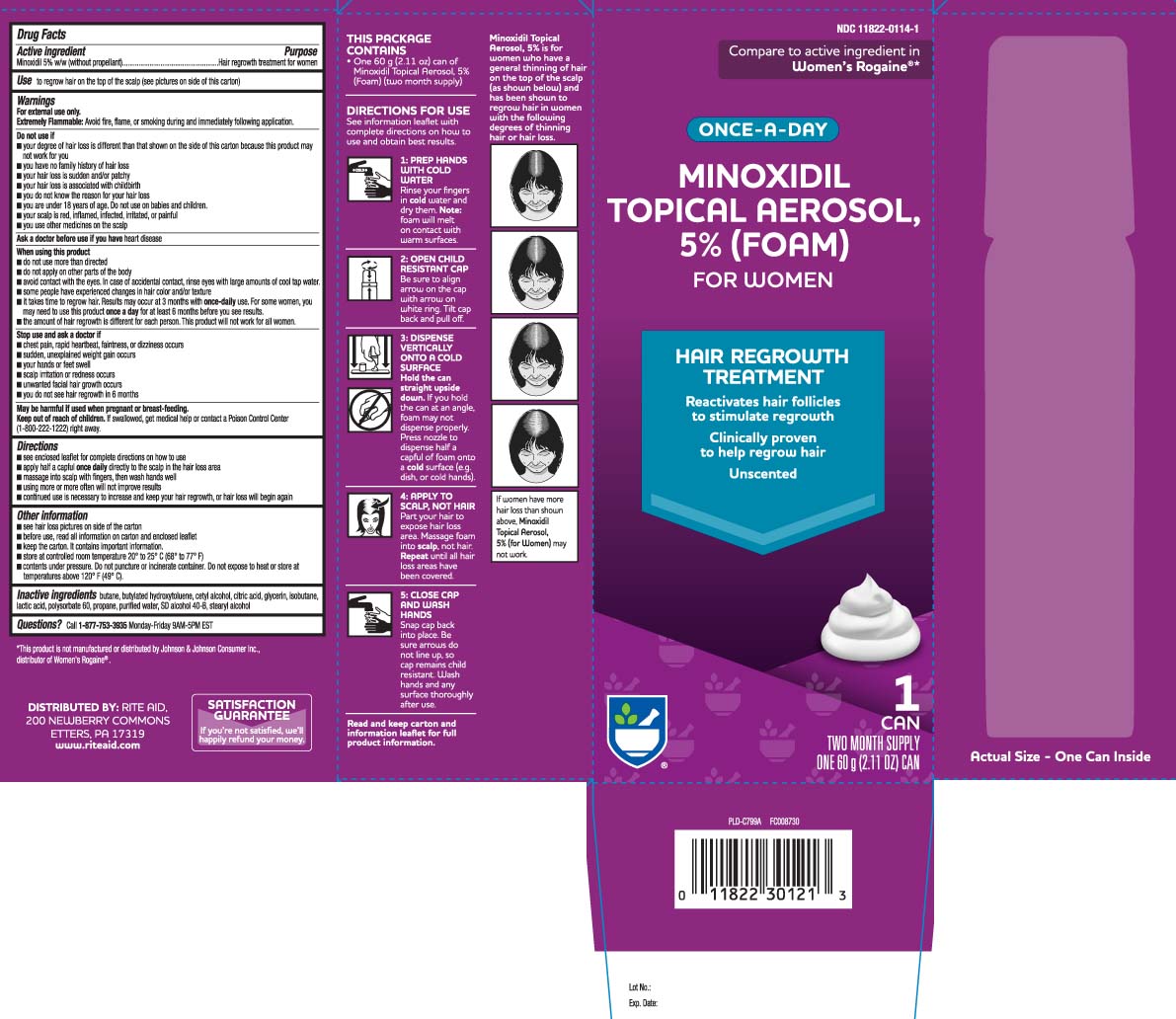 DRUG LABEL: Minoxidil
NDC: 11822-0114 | Form: AEROSOL, FOAM
Manufacturer: Rite Aid Corporation
Category: otc | Type: HUMAN OTC DRUG LABEL
Date: 20251118

ACTIVE INGREDIENTS: MINOXIDIL 50 mg/1 g
INACTIVE INGREDIENTS: BUTANE; BUTYLATED HYDROXYTOLUENE; CETYL ALCOHOL; ANHYDROUS CITRIC ACID; GLYCERIN; ISOBUTANE; LACTIC ACID; POLYSORBATE 60; PROPANE; WATER; ALCOHOL; STEARYL ALCOHOL

Minoxidil Topical Solution for Men

Active ingredient

Minoxidil 5% w/w (without propellant)

Purpose

Hair regrowth treatment for women

Use

to regrow hair on the top of the scalp (see pictures on side of this carton)

Warnings

For external use only.
Extremely Flammable: Avoid fire, flame, or smoking during and immediately following application.

Do not use if

- your degree of hair loss is different than that shown on the side of this carton because this product may not work for you
- you have no family history of hair loss
- your hair loss is sudden and/or patchy
- your hair loss is associated with childbirth
- you do not know the reason for your hair loss
- you are under 18 years of age. Do not use on babies and children.
- your scalp is red, inflamed, infected, irritated, or painful
- you use other medicines on the scalp

Ask a doctor before use if you have

heart disease

When using this product

- do not use more than directed
- do not apply on other parts of the body
- avoid contact with the eyes. In case of accidental contact, rinse eyes with large amounts of cool tap water.
- some people have experienced changes in hair color and/or texture
- it takes time to regrow hair. Results may occur at 3 months with once daily use For some women, you may need to use this product once a day for at least 6 months before you see results.
- the amount of hair regrowth is different for each person. This product will not work for all women.

Stop use and ask a doctor if

- chest pain, rapid heartbeat, faintness, or dizziness occurs
- sudden, unexplained weight gain occurs
- your hands or feet swell
- scalp irritation or redness occurs
- unwanted facial hair growth occurs
- you do not see hair regrowth in 6 months

Keep out of reach of children.

If swallowed, get medical help or contact a Poison Control Center (1-800-222-1222) right away.

Directions

- see enclosed leaflet for complete directions on how to use
- apply half a capful once daily directly to the scalp in the hair loss area
- massage into scalp with fingers, then wash hands well
- using more or more often will not improve results
- continued use is necessary to increase and keep your hair regrowth, or hair loss will begin again

Other information

- see hair loss pictures on side of this carton
- before use, read all information on carton and enclosed leaflet
- keep the carton. It contains important information.
- store at controlled room temperature 20º to 25ºC (68º to 77ºF)
- contents under pressure. Do not puncture or incinerate container. Do not expose to heat or store at temperature above 120ºF (49ºC).

Inactive ingredients

butane, butylated hydroxytoluene, cetyl alcohol, citric acid, glycerin, isobutane,lactic acid, polysorbate 60, propane, purified water, SD alcohol,40-Bstearyl alcohol

Questions?

Call 1-877-753-3935 Monday-Friday 9AM-5PM EST

Principal display panel

Compare to active ingredient in Women's Rogaine®*

ONCE-A-DAY

MINOXIDIL

TOPICAL AEROSOL,

5% (FOAM)

FOR WOMEN

HAIR REGROWTH TREATMENT

Reactivates hair follicles to stimulate regrowth

Clinical proven to help reqrow hair

Unscented

60 g (2.11OZ) CAN

*This product is not manufactured or distributed by Johnson & Johnson Consumer Inc., distributor of Women's Rogaine®.

DISTRIBUTED BY: RITE AID,

200 NEWBERRY COMMONS

ETTERS, PA 17319

www.riteaid.com

Package label

RITE AID Hair Regrowth Treatment